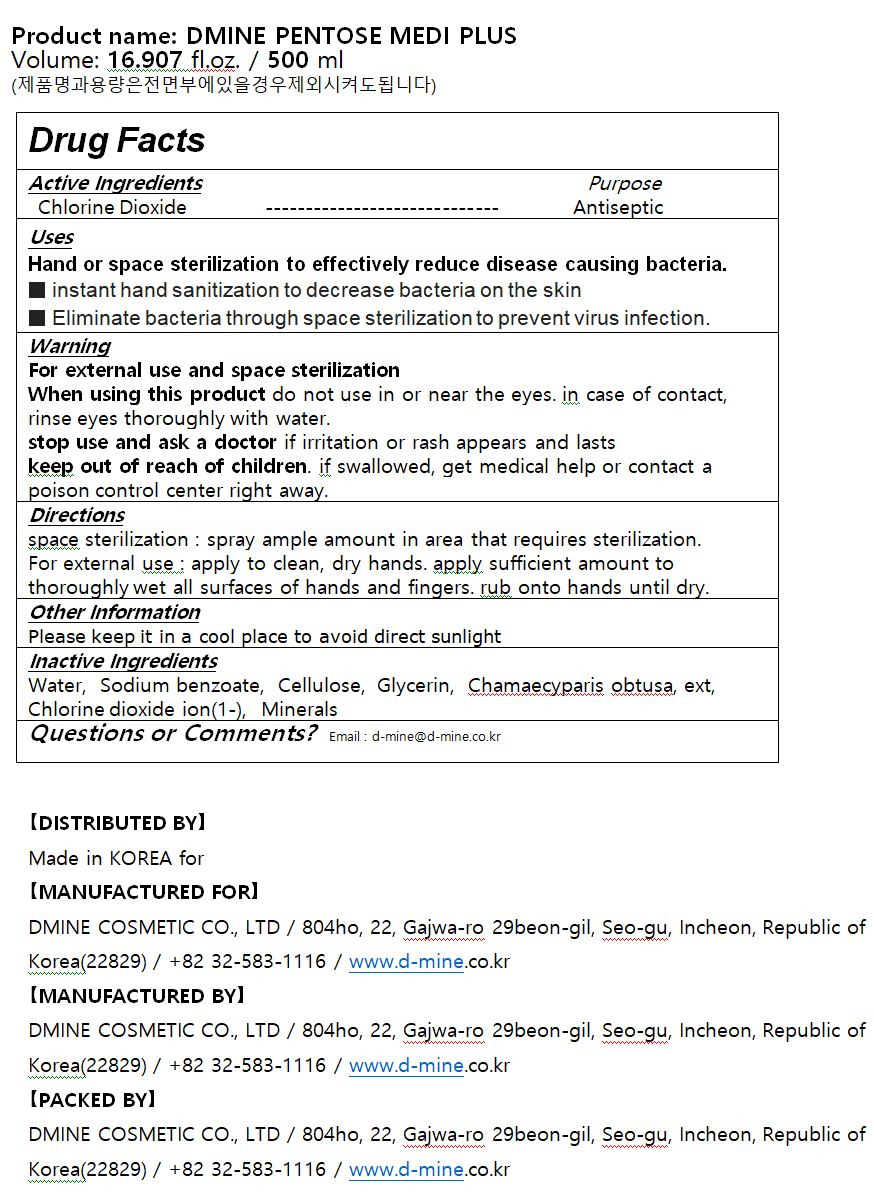 DRUG LABEL: DMINE PENTOSE MEDI PLUS
NDC: 79397-0001 | Form: LIQUID
Manufacturer: DMINE COSMETIC CO., LTD
Category: otc | Type: HUMAN OTC DRUG LABEL
Date: 20200722

ACTIVE INGREDIENTS: CHLORINE DIOXIDE 1 g/100 mL
INACTIVE INGREDIENTS: CHAMAECYPARIS OBTUSA LEAF; WATER; GLYCERIN; SODIUM BENZOATE

Drug Facts

ACTIVE INGREDIENT

Chlorine Dioxide

PURPOSE

Hand or space sterilization to effectively reduce disease causing bacteria.

■ instant hand sanitization to decrease bacteria on the skin

■ Eliminate bacteria through space sterilization to prevent virus infection.

KEEP OUT OF REACH OF THE CHILDREN

WARNINGS

■ Flammable. Keep away from fire or flame.

■ For external use only.

■ Do not use in eyes.

■ lf swallowed, get medical help promptly.

■ Stop use, ask doctor lf irritation occurs.

■ Keep out of reach of children.

DOSAGE AND ADMINISTRATION

for external use only

INACTIVE INGREDIENT

Water, Sodium benzoate, Cellulose, Glycerin, Chamaecyparis obtusa, ext, Chlorine dioxide ion(1-), Minerals

INDICATIONS AND USAGE

space sterilization : spray ample amount in area that requires sterilization.

For external use : apply to clean, dry hands. apply sufficient amount to thoroughly wet all surfaces of hands and fingers. rub onto hands until dry.